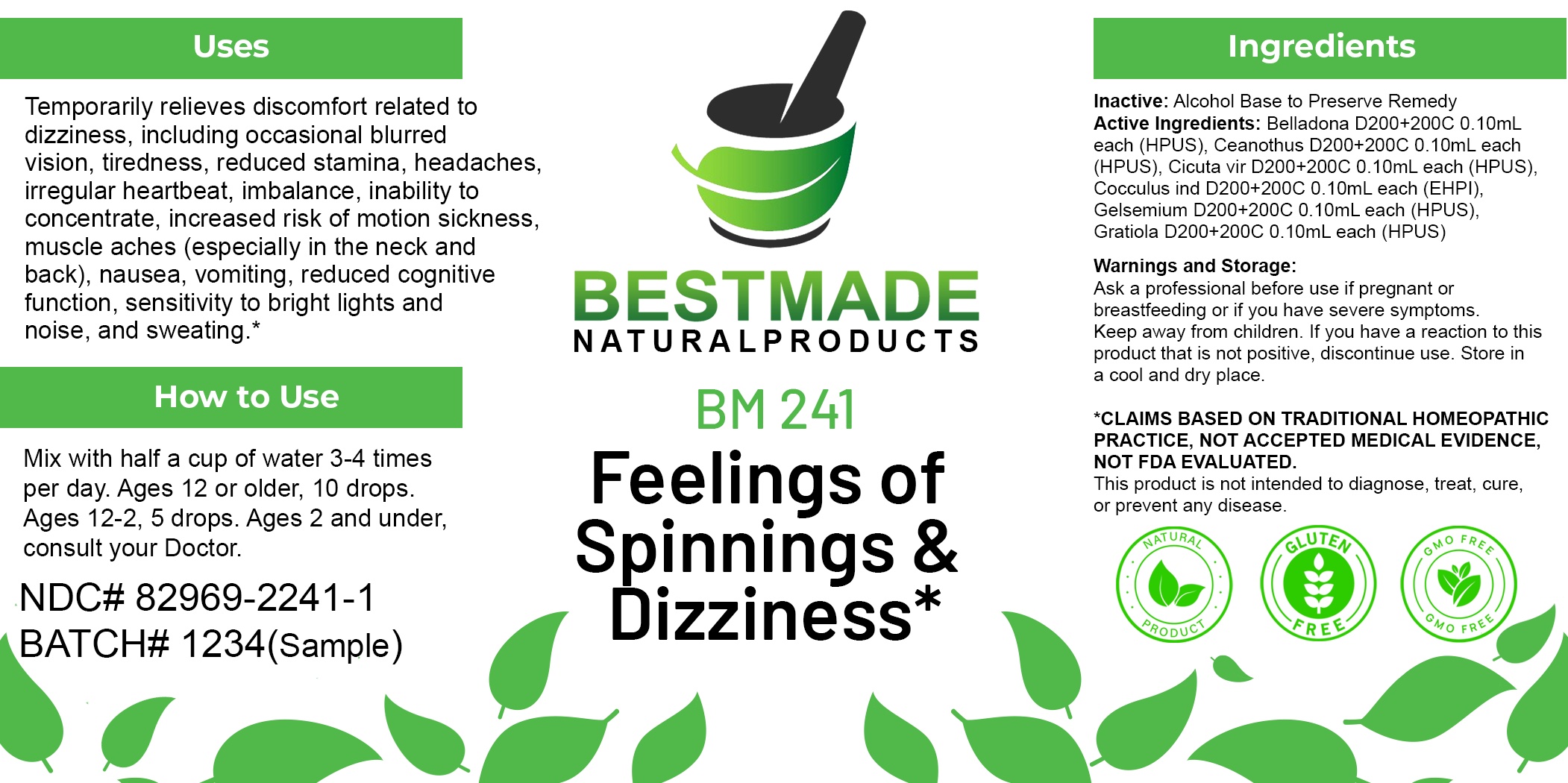 DRUG LABEL: Bestmade Natural Products BM241
NDC: 82969-2241 | Form: LIQUID
Manufacturer: Bestmade Natural Products
Category: homeopathic | Type: HUMAN OTC DRUG LABEL
Date: 20250304

ACTIVE INGREDIENTS: ATROPA BELLADONNA 30 [hp_C]/30 [hp_C]; CICUTA VIROSA ROOT 30 [hp_C]/30 [hp_C]; CEANOTHUS AMERICANUS LEAF 30 [hp_C]/30 [hp_C]; ANAMIRTA COCCULUS SEED 30 [hp_C]/30 [hp_C]; GELSEMIUM SEMPERVIRENS ROOT 30 [hp_C]/30 [hp_C]; GRATIOLA OFFICINALIS 30 [hp_C]/30 [hp_C]
INACTIVE INGREDIENTS: ALCOHOL 30 [hp_C]/30 [hp_C]

BM241

DOSAGE AND ADMINISTRATION

How to Use

Mix with half a cup of water 3-4 times per day. Ages 12 or older, 10 drops. Ages 12-2, 5 drops. Ages 2 and under, consult your Doctor.

Inactive:

Alcohol Base to Preserve Product

ACTIVE INGREDIENT

Active Ingredients: Belladona D200+200C 0.10mL each (HPUS), Ceanothus D200+200C 0.10mL each (HPUS), Cicuta vir D200+200C 0.10mL each (HPUS), Cocculus ind D200+200C 0.10mL each (EHPI), Gelsemium D200+200C 0.10mL each (HPUS), Gratiola D200+200C 0.10mL each (HPUS)

KEEP OUT OF REACH OF CHILDREN

Warnings and Storage:

Ask a professional before use if pregnant or breastfeeding or if you have severe symptoms.

Keep away from children. If you have a reaction to this product that is not positive, discontinue use. Store in a cool and dry place

*CLAIMS BASED ON TRADITIONAL HOMEOPATHIC PRACTICE, NOT ACCEPTED MEDICAL EVIDENCE NOT FDA EVALUATED.
This product is not intended to diagnose, treat, cure, or prevent any disease.

Warnings and Storage:

Ask a professional before use if pregnant or breastfeeding or if you have severe symptoms.

Keep away from children. If you have a reaction to this product that is not positive, discontinue use. Store in a cool and dry place

*CLAIMS BASED ON TRADITIONAL HOMEOPATHIC PRACTICE, NOT ACCEPTED MEDICAL EVIDENCE NOT FDA EVALUATED.
This product is not intended to diagnose, treat, cure, or prevent any disease.

Uses
Temporarily relieves discomfort related to dizziness, including occasional blurred vision, tiredness, reduced stamina, headaches,
irregular heartbeat, imbalance, inability to concentrate, increased risk of motion sickness, muscle aches (especially in the neck and
back), nausea, vomiting, reduced cognitive function, sensitivity to bright lights and noise, and sweating.*

Uses
Temporarily relieves discomfort related to dizziness, including occasional blurred vision, tiredness, reduced stamina, headaches,
irregular heartbeat, imbalance, inability to concentrate, increased risk of motion sickness, muscle aches (especially in the neck and
back), nausea, vomiting, reduced cognitive function, sensitivity to bright lights and noise, and sweating.*

Entire package label